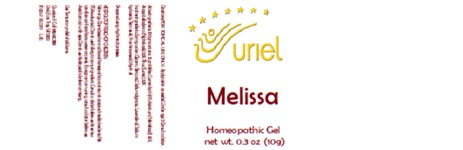 DRUG LABEL: Melissa
NDC: 48951-7222 | Form: GEL
Manufacturer: Uriel Pharmacy, Inc
Category: homeopathic | Type: HUMAN OTC DRUG LABEL
Date: 20250916

ACTIVE INGREDIENTS: MELISSA OFFICINALIS 1 [hp_X]/1 g; ACONITUM NAPELLUS 30 [hp_X]/1 g; TOXICODENDRON PUBESCENS LEAF 30 [hp_X]/1 g; ATROPA BELLADONNA 30 [hp_X]/1 g
INACTIVE INGREDIENTS: TEA TREE OIL; SODIUM HYDROXIDE; GLYCERIN; LAVENDER OIL; BORIC ACID; SODIUM ALGINATE; FRANKINCENSE OIL; WATER; MYRRH OIL

Melissa

INDICATIONS AND USAGE

Directions: FOR TOPICAL USE ONLY.

DOSAGE AND ADMINISTRATION

Apply to skin as needed. Under age 2: Consult a doctor.

ACTIVE INGREDIENT

Active Ingredients: 100 gm contains: 35 gm Melissa (Lemon balm) 1X; Aconitum (Monkshood) 30X, Atropa belladonna (Nightshade) 30X, Rhus (Sumac) 30X

INACTIVE INGREDIENT

Inactive Ingredients: Spring water, Glycerin, Boric acid, Sodium alginate, Lavender oil, Sodium hydroxide, Tea tree oil, Frankincense oil, Myrrh oil

Prepared using rhythmical processes.

PURPOSE

Use: Temporary relief of cold sores.

KEEP OUT OF REACH OF CHILDREN.

WARNINGS

Warnings: Claims based on traditional homeopathic practice, not accepted medical evidence. Not FDA evaluated. Do not use if allergic to any ingredient. Consult a doctor before use for serious conditions or if conditions worsen or persist. If pregnant or nursing, consult a doctor before use. Avoid contact with eyes. Do not use if safety seal is broken or missing.

Questions? Call 866.642.2858
Uriel, East Troy, WI 53120
shopuriel.com Lot: